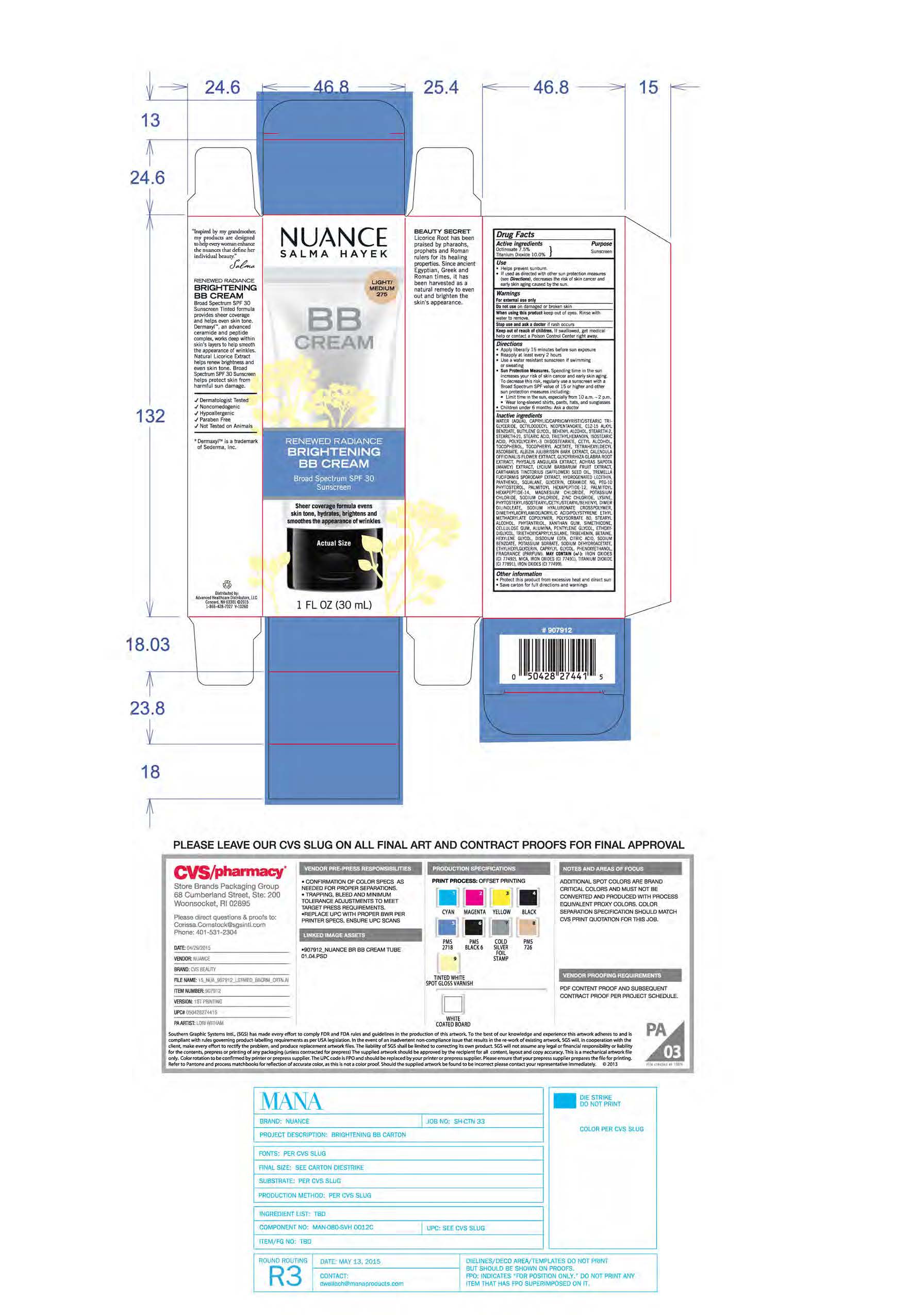 DRUG LABEL: Nuance Salma Hayek Renewed Radiance Brightening BB Cream Broad Spectrum SPF 30 Sunscreen
NDC: 69842-801 | Form: LOTION
Manufacturer: CVS Pharmacy, Inc
Category: otc | Type: HUMAN OTC DRUG LABEL
Date: 20170118

ACTIVE INGREDIENTS: OCTINOXATE 7.5 g/100 g; TITANIUM DIOXIDE 10 g/100 g
INACTIVE INGREDIENTS: WATER; CAPRYLIC/CAPRIC/PALMITIC/STEARIC TRIGLYCERIDE; OCTYLDODECYL NEOPENTANOATE; C12-15 ALKYL LACTATE; BUTYLENE GLYCOL; BEHENYL BENZOATE; STEARETH-2; STEARETH-21; STEARIC ACID; TRIETHYLHEXANOIN; ISOSTEARIC ACID; POLYGLYCERYL-3 DIISOSTEARATE; CETYL ALCOHOL; TOCOPHEROL; .ALPHA.-TOCOPHEROL ACETATE; TETRAHEXYLDECYL ASCORBATE; ALBIZIA JULIBRISSIN BARK; CALENDULA OFFICINALIS FLOWER; GLYCYRRHIZA GLABRA; PHYSALIS ANGULATA; LYCIUM BARBARUM FRUIT; CARTHAMUS TINCTORIUS FLOWER OIL; TREMELLA FUCIFORMIS WHOLE; HYDROGENATED SOYBEAN LECITHIN; PANTHENOL; SQUALANE; GLYCERIN; CERAMIDE NG; PEG-10 .BETA.-SITOSTEROL; PALMITOYL HEXAPEPTIDE-12; MAGNESIUM CHLORIDE; POTASSIUM CHLORIDE; SODIUM CHLORIDE; ZINC CHLORIDE; LYSINE; PEG-9 DIGLYCIDYL ETHER/SODIUM HYALURONATE CROSSPOLYMER; N,N-DIMETHYLACRYLAMIDE; POLYSORBATE 80; STEARYL ALCOHOL; PHYTANTRIOL; XANTHAN GUM; CELLULOSE ACETATE; PENTYLENE GLYCOL; ETHOXYDIGLYCOL BEHENATE; TRIETHOXYCAPRYLYLSILANE; TRIBEHENIN; BETAINE; HEXYLENE GLYCOL; DISODIUM EDTA-COPPER; ANHYDROUS CITRIC ACID; SODIUM BENZOATE; POTASSIUM SORBATE; SODIUM DEHYDROACETATE; ETHYLHEXYLGLYCERIN; CAPRYLYL GLYCOL; PHENOXYETHANOL

DRUG FACTS

Active Ingredients

Octinoxate 7.50%

Titanium Dioxide 10%

Use

- Helps prevent sunburn.
- If used as directed with other sun protection measures (see Directions), decreases the risk of skin cancer and early skin aging caused by the sun.

Warnings

- For external use only
- Do not use on damaged or broken skin
- When using this product keep out of eyes. Rinse with water to remove.
- Stop use and ask a docor if rash occurs
- Keep out of reach of children. If swalled, get medical help or contact a Poison Control Center right away.

Directions

- Apply liberally 15 minutes before sun exposure
- Reapply at least every 2 hours
- Use water resistant sunscreen if swimming or sweathing
- Sun Protection Measures: Spending time in the sun decreases risk of skin cancer and early again. To decrease this risk, regulaory use a sunscreen with a Broad Spectrum SPF value of 15 or higher and other sun protection measures including: Limit time in the sun especially from 10:00 am - 2:00 pm. Wear long sleeved shirts, pants, hats and sunglasses.
- Children under 6 months: ask a doctor

Inactive Ingredients

WATER (AQUA), CAPRYLIC./CAPRIC/MYRISTIC/STEARIC TRIGLYCERIDE,
OCTYLDODECYL NEOPENTANOATE, Cl2-15 ALKYL
BENZOATE, BUffiENE GLYCOL, BEHENYL ALCOHOL, STEARETH-2,
STEARETH-21, STEARIC ACID, TRIETHYLHEXANOIN, ISOSTEARIC
ACID, POLYGLYCERYL-3 DIISOSTEARATE, CETYL ALCOHOL,
TOCOPHEROL, TOCOPHERYL ACETATE, TETRAHEXYLOECYL
ASCORBATE, ALBIZIA JULIBRISSIN BARK EXTRACT, CALENDULA
OFFICINALIS FLOWER EXTRACT, GLYCYRRHIZA GLABRA ROOT
EXTRACT, PHYSALIS ANGULATA EXTRACT, ACHRAS SAPOTA
(MAMEY) EXTRACT, LYCIUM BARBARUM FRUIT EXTRACT,
CARTHAMUS TINCTORIUS (SAFFLOWER) SEED OIL, TREMELLA
FUCIFORMIS SPOROCARP EXTRACT, HYDROGENATED LECITH IN,
PANTHENOL, SQUALANE, GLYCERIN, CERAMIDE NG, PEG-10
PHYTOSTEROL, PALMITOYL HEXAPEPTIDE-12, PALMITOYL
HEXAPEPTIDE-14, MAGNESIUM CHLORIDE, POTASSIUM
CHLORIDE, SODIUM CHLORIDE, ZINC CHLORIDE, LYSINE,
PHYTDSTERYUISOSTEARYL/CETYUSTEARYUBEHENYL DIMER
DILINOLEATE, SODIUM HYALURONATE CROSSPOLYMER,
DIMETHYLACRYLAMIDE/ACRYLIC ACID/POLYSTYRENE ETHYL
METHACRYLATE COPOLYMER, POLYSORBATE 80, STEARYL
ALCOHOL, PHYTANTRIOL, XANTHAN GUM, SIMETHICONE,
CELLULOSE GUM, ALUMINA, PENTYLENE GLYCOL, ETHOXYDIGLYCOL,
TRIETHOXYCAPRYLYLSILANE, TRIBEHEN IN, BETAINE,
HEXYLENE GLYCOL, DISODIUM EDTA, CITRIC ACID, SODIUM
BENZOATE, POTASSIUM SORBATE, SODIUM DEHYDROACETATE,
ETHYLHEXYLGLYCERIN, CAPRYLYL GLYCOL, PHENOXYETHANOL,
FRAGRANCE (PARFUM). MAY CONTAIN C+/·l: IRON OXIDES
(Cl 77492), MICA, IRON OXIDES (Cl 77491), TITANIUM DIOXIDE
(Cl 77891), IRON OXIDES (Cl 77499).

Other Information

- Protect this product form excessive heat and direct sun
- Save Carton for full directions and warnings